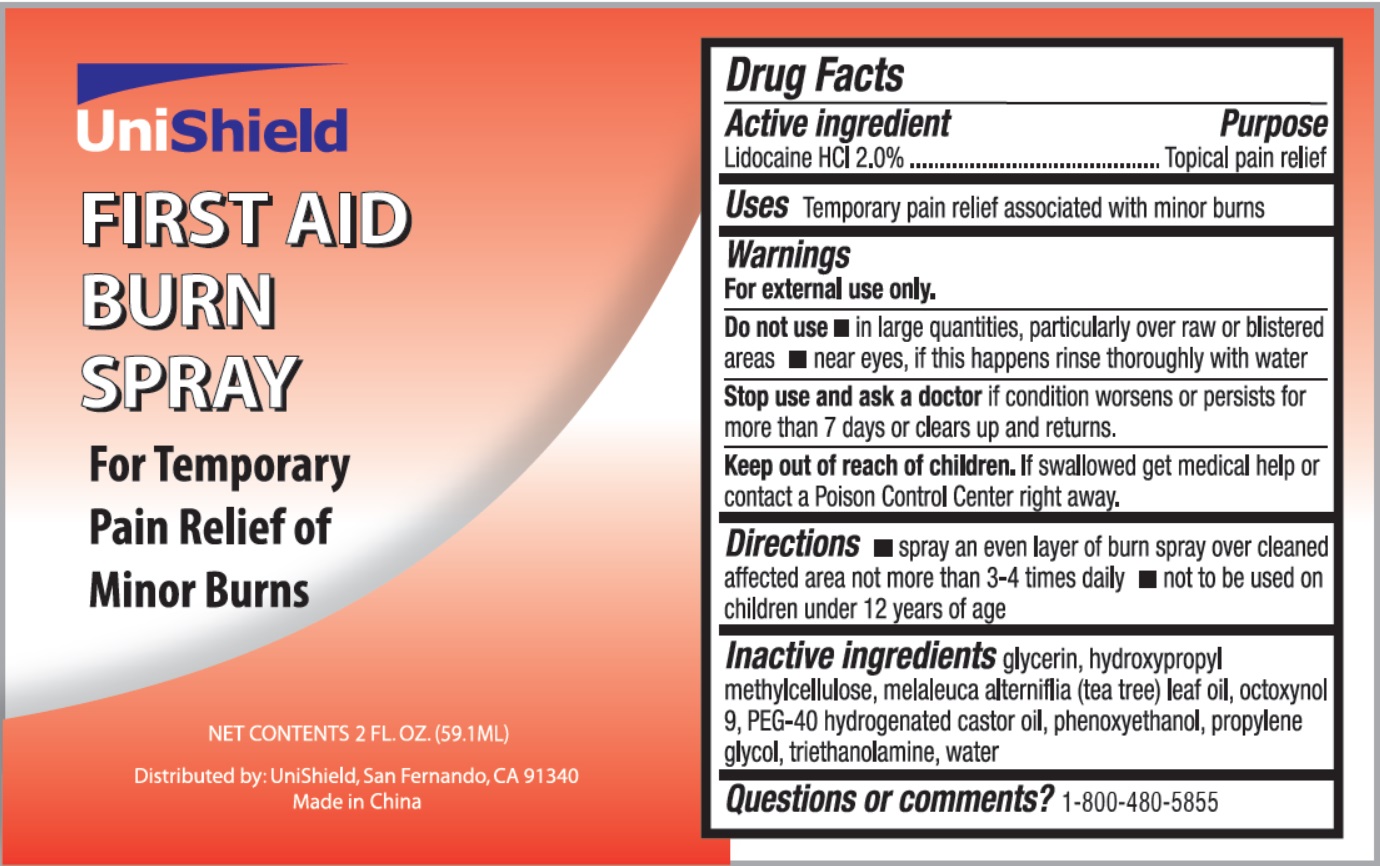 DRUG LABEL: UniShield First Aid Burn
NDC: 49314-0002 | Form: SPRAY
Manufacturer: Unishield
Category: otc | Type: HUMAN OTC DRUG LABEL
Date: 20250928

ACTIVE INGREDIENTS: LIDOCAINE HYDROCHLORIDE 20 mg/1 mL
INACTIVE INGREDIENTS: HYPROMELLOSES; WATER; GLYCERIN; TEA TREE OIL; POLYOXYL 40 HYDROGENATED CASTOR OIL; PHENOXYETHANOL; PROPYLENE GLYCOL; TROLAMINE; OCTOXYNOL 9

49314-0002-1 Unishield First Aid Burn Spray

Active ingredient

Lidocaine HCL 2.0%

Purpose

.Topical pain relief

Uses

Temporary pain relief associated with minor burns

Warnings

For external use only

Do not use

- in large quantities, particularly over raw or blistered areas.
- near eyes, if this happens rinse thoroughly with water

Stop use and ask a doctor

if condition worsens or persists for more than 7 days or clears up and returns.

Keep out of reach of children.

If swallowed, get medical help or contact a Poison Control Center right away.

Directions

- spray an over layer of burn spray over cleaned affected area not more than 3-4 times daily
- not to be used on children under 12 years of age

Inactive ingredients

glycerin, hydroxypropyl methylcellulose, melaleuca alterniflia (tea tree) leaf oil, octoxynol 9, PEG-40 hydrogenated castor oil, phenoxyethanol, propylene glycol, triethanolamine, water

Questions or comments？

1-800-480-5855